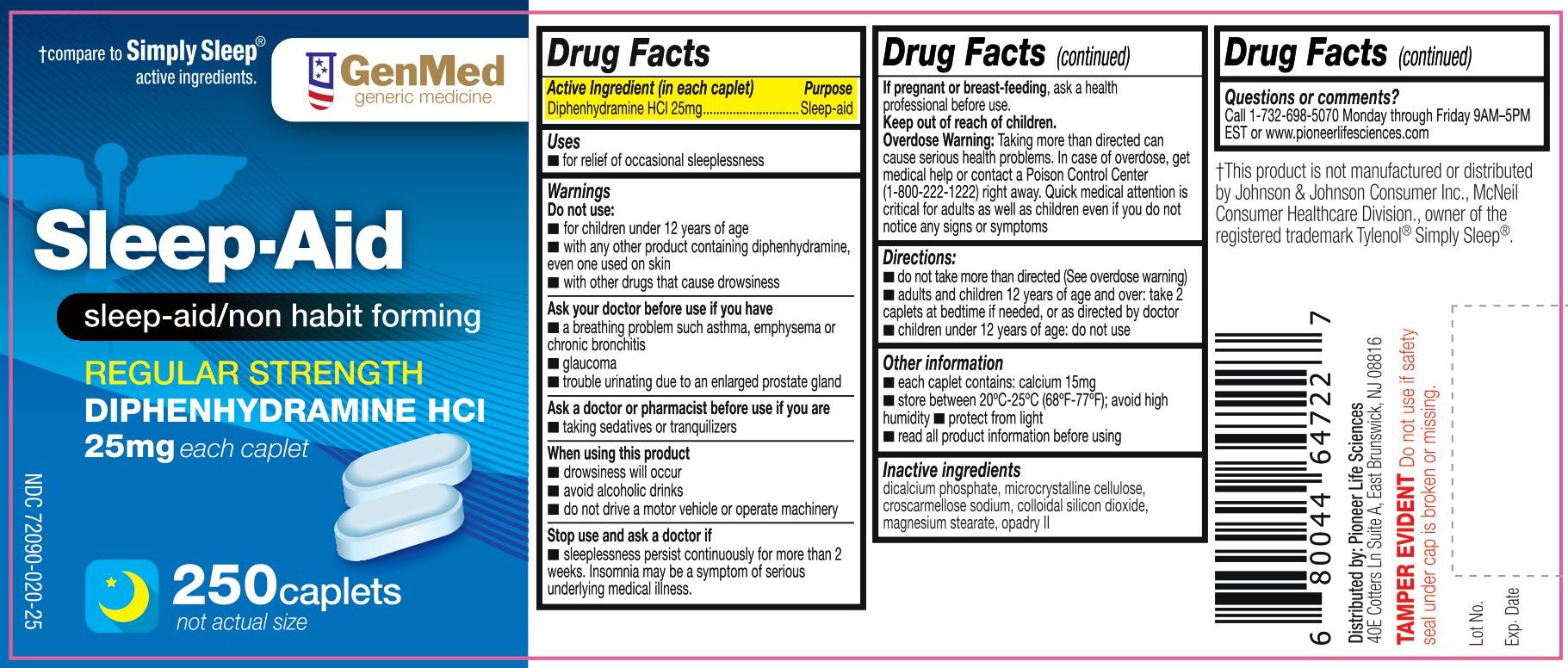 DRUG LABEL: Sleep Aid
NDC: 72090-020 | Form: TABLET
Manufacturer: Pioneer Life Sciences, LLC
Category: otc | Type: HUMAN OTC DRUG LABEL
Date: 20180723

ACTIVE INGREDIENTS: DIPHENHYDRAMINE HYDROCHLORIDE 25 mg/1 1
INACTIVE INGREDIENTS: CALCIUM PHOSPHATE, DIBASIC, ANHYDROUS; MICROCRYSTALLINE CELLULOSE; CROSCARMELLOSE SODIUM; SILICON DIOXIDE; MAGNESIUM STEARATE; POLYVINYL ALCOHOL; TALC; TITANIUM DIOXIDE; POLYETHYLENE GLYCOL; D&C RED NO. 27 ALUMINUM LAKE; LECITHIN, SOYBEAN

Diphenhydramine HCl 25 mg

Drug Facts Active ingredient (in each caplet)

Diphenhydramine HCl 25 mg

Purpose

Sleep-aid

Uses

- for relief of occasional sleeplessness

Warnings

Do not use

- for children under 12 years of age
- with any other product containing diphenhydramine, even one used on skin
- with other drugs that cause drowsiness

Ask your doctor before use if you have

- a breathing problem such as emphysema or chronic bronchitis
- glaucoma
- trouble urinating due to an enlarged prostate gland

Ask a doctor or pharmacist before use if you are

- taking sedative or tranquilizers

When using this product

- drowsiness will occur
- avoid alcoholic drinks
- do not drive a motor vehicle or operating machinery

Stop use and ask a doctor if

- sleeplessness persists continuously for more than 2 weeks. Insomnia may be a symptom of a serious underlying medical illness.

If pregnant or breast-feeding,

ask a health professional before use.

Keep out of reach of children.

Overdose Warning: Taking more than directed can cause serious health problems. In case of overdose, get medical help or contact a Poison Control Center (1-800-222-1222) right away. Quick medical attention is critical for adults as well as for children even if you do not notice any signs or symptoms.

Directions

- do not take more than directed (see overdose warning)
- adults and children 12 years of age and over: - take 2 caplets at bedtime if needed, or as directed by a doctor
- children under 12 years of age: do not use

Other information

- each caplet contains: calcium 15 mg
- store between 20°-25°C (68°-77°F); avoid high humidity
- protect from light
- read all product information before using

Inactive ingredients

dicalcium phosphate, microcrystalline cellulose, croscarmellose sodium, colloidal silicon dioxide, magnesium stearate, opadry II

Questions or comments?

Call 1-732-698-5070 Monday through Friday 9AM–5PM EST or www.pioneerlifesciences.com

Distributed by:
Pioneer Life Sciences
40E Cotters Lane, Suite A
East Brunswick, NJ 08816